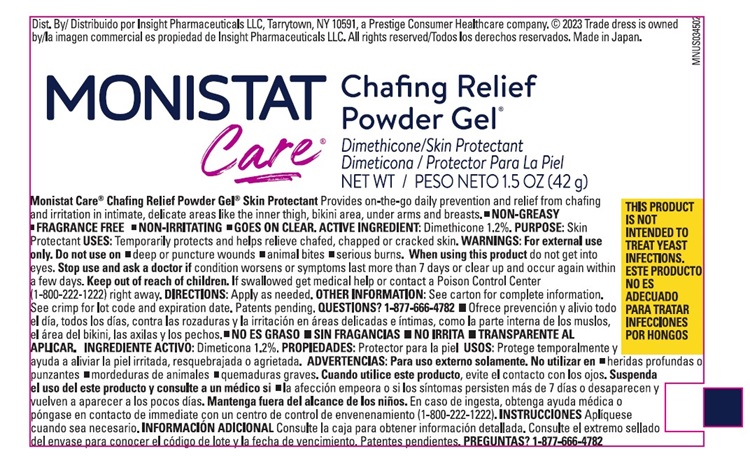 DRUG LABEL: Monistat Complete Care Chafing Relief
NDC: 57501-087 | Form: GEL
Manufacturer: Apex International Mfg., LLC
Category: otc | Type: HUMAN OTC DRUG LABEL
Date: 20240618

ACTIVE INGREDIENTS: DIMETHICONE 1.2 g/100 g
INACTIVE INGREDIENTS: CYCLOMETHICONE 5; DIMETHICONE/VINYL DIMETHICONE CROSSPOLYMER (SOFT PARTICLE); SILICA DIMETHYL SILYLATE; VINYL DIMETHICONE/METHICONE SILSESQUIOXANE CROSSPOLYMER

Monistat Chafing Gel

Monistat Care Chafing Relief Powder Gel®

Drug Facts

Active ingredient

Dimethicone 1.2%

Purpose

Skin Protectant

Use

- Temporarily protects and helps relieve chafed, chapped or cracked skin.

Warnings

For external use only.

Do not use on

- deep or puncture wounds
- animal bites
- serious burns

When using this product

do not get into eyes.

Stop use and ask a doctor if

- condition worsens
- symptoms last more than 7 days or clear up and occur again within a few days

Keep out of reach of children.

If swallowed get medical help or contact a Poison Control Center (1-800-222-1222) right away.

Directions

Apply as needed.

Other information

Store at 20˚-25˚C (68˚-77˚F)

Inactive ingredients

cyclomethicone, dimethicone, dimethicone/vinyl dimethicone crosspolymer, silica dimethyl silylate, vinyl dimethicone/methicone silsesquioxane crosspolymer

Questions?

1-877-666-4782 Monistat.com

PRINCIPAL DISPLAY PANEL

MONISTAT
Care®
Chafing Relief
Powder Gel®
Dimethicone/Skin Protectant
Dimeticona / Protector Para La Piel
NET WT / PESA NETO 1.5 oz (42g)